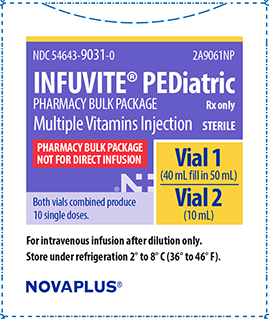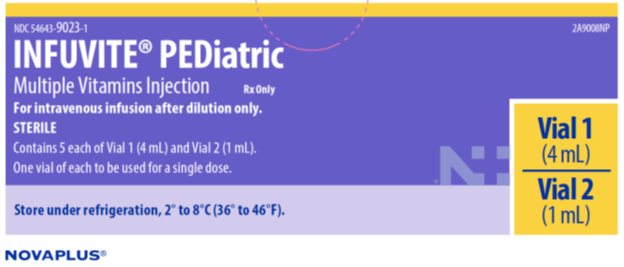 DRUG LABEL: Pediatric Infuvite Multiple Vitamins
NDC: 54643-9031 | Form: KIT | Route: INTRAVENOUS
Manufacturer: Sandoz Inc
Category: prescription | Type: HUMAN PRESCRIPTION DRUG LABEL
Date: 20250818

ACTIVE INGREDIENTS: ASCORBIC ACID 80 mg/4 mL; VITAMIN A PALMITATE 2300 [iU]/4 mL; CHOLECALCIFEROL 400 [iU]/4 mL; THIAMINE HYDROCHLORIDE 1.2 mg/4 mL; RIBOFLAVIN 5'-PHOSPHATE SODIUM 1.4 mg/4 mL; PYRIDOXINE HYDROCHLORIDE 1 mg/4 mL; NIACINAMIDE 17 mg/4 mL; DEXPANTHENOL 5 mg/4 mL; .ALPHA.-TOCOPHEROL ACETATE 7 [iU]/4 mL; PHYTONADIONE 0.2 mg/4 mL; FOLIC ACID 140 ug/1 mL; BIOTIN 20 ug/1 mL; CYANOCOBALAMIN 1 ug/1 mL
INACTIVE INGREDIENTS: POLYSORBATE 80 50 mg/4 mL; SODIUM HYDROXIDE; HYDROCHLORIC ACID; WATER; MANNITOL 75 mg/1 mL; ANHYDROUS CITRIC ACID; SODIUM CITRATE, UNSPECIFIED FORM; WATER

HIGHLIGHTS OF PRESCRIBING INFORMATION

These highlights do not include all the information needed to use INFUVITE PEDIATRIC safely and effectively. See full prescribing information for INFUVITE PEDIATRIC.
INFUVITE PEDIATRIC (multiple vitamins injection), for intravenous use
Initial U.S. Approval: 2001

1 INDICATIONS AND USAGE

INFUVITE PEDIATRIC is a combination of vitamins indicated for the prevention of vitamin deficiency in pediatric patients up to 11 years of age receiving parenteral nutrition (1)

2 DOSAGE AND ADMINISTRATION

- INFUVITE PEDIATRIC is a combination product that contains the following vitamins: ascorbic acid, vitamin A, vitamin D, thiamine, riboflavin, pyridoxine, niacinamide, dexpanthenol, vitamin E, vitamin K1, folic acid, biotin, and vitamin B12 (2.1)
- INFUVITE PEDIATRIC is for administration by intravenous infusion after dilution (2.1)
- Recommended daily dosage is based on patient’s actual weight (2.2):
  - INFUVITE PEDIATRIC Single Dose:
    - Weight less than 1 kg: 1.2 mL of Vial 1 and 0.3 mL of Vial 2
    - Weight 1 kg to less than 3 kg: 2.6 mL of Vial 1 and 0.65 mL Vial 2
    - Weight 3 kg or greater: 4 mL of Vial 1 and 1 mL of Vial 2
  - INFUVITE PEDIATRIC Pharmacy Bulk Package:
    - Weight less than 1 kg: 1.5 mL of combined content of Vials 1 and 2
    - Weight 1 kg to less than 3 kg: 3.25 mL of combined content of Vials 1 and 2
    - Weight 3 kg or greater: 5 mL of combined content of Vials 1 and 2.
- Supplemental vitamin A may be required for low-birth weight infants (2.2)
- INFUVITE PEDIATRIC is supplied as a single dose and as a pharmacy bulk package:
  - Single Dose consists of two vials labeled Vial 1 and Vial 2. Add one daily dose of Vial 1 and one daily dose of Vial 2 directly to at least 100 mL of intravenous dextrose or saline solution prior to intravenous use (2.3)
  - Pharmacy Bulk Package consists of two vials labeled Vial 1 and Vial 2. Transfer contents of Vial 2 to contents of Vial 1. Then, take 1.5 mL, 3.25 mL, or 5 mL from mixture and add to at least 100 mL of intravenous dextrose or saline solution prior to intravenous use (2.3)
- After dilution in an intravenous infusion, refrigerate resulting solution unless used immediately. Use solution within 24 hours after dilution (2.3)
- Monitor blood vitamin concentrations (2.4)
- See Full Prescribing Information for drug incompatibilities (2.5).

3 DOSAGE FORMS AND STRENGTHS

- INFUVITE PEDIATRIC single dose is an injection consisting of two vials labeled Vial 1 (4 mL) and Vial 2 (1 mL) (3)
- INFUVITE PEDIATRIC pharmacy bulk package is an injection consisting of two vials labeled Vial 1 (50 mL) and Vial 2 (10 mL) (3)
- See Full Prescribing Information for vitamin strengths (11)

4 CONTRAINDICATIONS

- Hypersensitivity to any of vitamins or excipients (4)
- Existing hypervitaminosis (4)

5 WARNINGS AND PRECAUTIONS

- Risk of Aluminum Toxicity: For at risk patients (renal failure or those with prolonged therapy), consider periodic monitoring of aluminum levels (5.1)
- Allergic Reactions: To thiamine may occur (5.2)
- Hypervitaminosis A: Patients with renal failure or liver disease may be at higher risk (5.3)
- Decreased Anticoagulant Effect of Warfarin: Monitor INR (5.4, 7.1)
- Interferes with Megaloblastic Anemia Diagnosis: Avoid during testing for this disorder (5.5)
- Risk of Vitamin Deficiencies or Excesses: Monitor blood vitamin concentrations (5.6)
- False Negative Urine Glucose Tests: Due to vitamin C (5.7)
- Risk of Vitamin E Toxicity: Additional oral and parenteral vitamin E may result in elevated vitamin E blood concentrations in infants (5.8)
- Low Vitamin A Levels: Monitor vitamin A levels (5.9)
- Risk of E-Ferol Syndrome: Due to polysorbates (5.10)

6 ADVERSE REACTIONS

Adverse reactions have included anaphylaxis, rash, erythema, pruritis, headache, dizziness, agitation, anxiety, diplopia (6)

To report SUSPECTED ADVERSE REACTIONS, contact Sandoz Inc. at 1-800-525-8747 or FDA at 1-800-FDA-1088 or www.fda.gov/medwatch.

7 DRUG INTERACTIONS

Effect of INFUVITE PEDIATRIC on other drugs:

- Antibiotics: Thiamine, riboflavin, pyridoxine, niacinamide, and ascorbic acid decrease activities of erythromycin, kanamycin, streptomycin, doxycycline, and lincomycin (7.1)
- Bleomycin: Ascorbic acid and riboflavin may reduce the activity of bleomycin (7.1)
- Levodopa: Pyridoxine may decrease blood levels of levodopa and levodopa efficacy may decrease (7.1)
- Phenytoin: Folic acid may decrease phenytoin blood levels and increase risk of seizure activity (7.1)
- Methotrexate: Folic acid may decrease response to methotrexate (7.1)

Effects of other drugs on INFUVITE PEDIATRIC:

- Hydralazine, Isoniazid: Concomitant administration of hydralazine or isoniazid may increase pyridoxine requirements (7.2).
- Phenytoin: May decrease folic acid concentrations (7.2)

8 USE IN SPECIFIC POPULATIONS

- Renal Impairment: Monitor renal function, calcium, phosphorus and vitamin A levels (8.6)
- Hepatic Impairment: Monitor vitamin A levels (8.7)

FULL PRESCRIBING INFORMATION

1 INDICATIONS AND USAGE

INFUVITE PEDIATRIC is a combination of vitamins indicated for the prevention of vitamin deficiency in pediatric patients up to 11 years of age receiving parenteral nutrition.

The physician should not await the development of clinical signs of vitamin deficiency before initiating vitamin therapy.

2 DOSAGE AND ADMINISTRATION

2.1 Important Dosage Instructions

INFUVITE PEDIATRIC is a combination product that contains the following vitamins: ascorbic acid, vitamin A, vitamin D, thiamine, riboflavin, pyridoxine, niacinamide, dexpanthenol, vitamin E, vitamin K1, folic acid, biotin, and vitamin B12.

INFUVITE PEDIATRIC is supplied as a single dose or as a pharmacy bulk package, for intravenous use intended for administration by intravenous infusion after dilution:

- INFUVITE PEDIATRIC Single Dose consists of two vials. A weight-based volume from each vial must be added directly to dextrose or saline solution prior to intravenous administration [see Dosage and Administration (2.2, 2.3)].
- INFUVITE PEDIATRIC Pharmacy Bulk Package consists of two pharmacy bulk vials which must be mixed prior to use. The mixed solution will provide multiple daily doses which must be diluted prior to intravenous administration. Pharmacy bulk package of INFUVITE PEDIATRIC is intended for dispensing of single doses to multiple patients in a pharmacy admixture program and is restricted to the preparation of admixtures for infusion. [see Dosage and Administration (2.2, 2.3)].

2.2 Dosage Information

The recommended daily dosage volume is based on the patient's actual weight less than 1 kg, 1 kg to less than 3 kg, and 3 kg or greater.

Patients with multiple vitamin deficiencies or with increased vitamin requirements may need multiple daily dosages as indicated or additional doses of individual vitamins. Supplemental vitamin A may be required for low-birth weight infants.

Additional daily dosages of Vitamin E in infants are not recommended [see Warnings and Precautions (5.8)].

INFUVITE PEDIATRIC Single Dose (see Table 1):

One daily dose of Vial 1 (1.2 mL, 2.6 mL or 4 mL) and one daily dose of Vial 2 (0.3 mL, 0.65 mL or 1 mL) based on the patient’s weight are added directly to a specified volume of an intravenous fluid [see Dosage and Administration (2.3)] (see Table 1).

Table 1: Recommended Weight-Based Dosage of INFUVITE PEDIATRIC Single Dose
 | Less than 1 kg | 1 kg to less than 3 kg | 3 kg or greater
Daily Dosage Volume – Vial 1 | 1.2 mL | 2.6 mL | 4 mL
Ascorbic acid (Vitamin C) | 24 mg | 52 mg | 80 mg
Vitamin A (as palmitate) | 690 IU (equals 0.2 mg) | 1495 IU (equals 0.5 mg) | 2,300 IU (equals 0.7 mg)
Vitamin D3 (cholecalciferol) | 120 IU (equals 3 mcg) | 260 IU (equals 7 mcg) | 400 IU (equals 10 mcg)
Thiamine (Vitamin B1) (as the hydrochloride) | 0.4 mg | 0.8 mg | 1.2 mg
Riboflavin (Vitamin B2) (as riboflavin 5-phosphate sodium) | 0.4 mg | 0.9 mg | 1.4 mg
Pyridoxine HCl (Vitamin B6) | 0.3 mg | 0.7 mg | 1 mg
Niacinamide | 5.1 mg | 11.1 mg | 17 mg
Dexpanthenol (as d-pantothenyl alcohol) | 1.5 mg | 3.3 mg | 5 mg
Vitamin E (dl-α-tocopheryl acetate) | 2.1 IU (equals 2 mg) | 4.6 IU (equals 5 mg) | 7 IU (equals 7 mg)
Vitamin K1 | 0.1 mg | 0.1 mg | 0.2 mg
Daily Dosage Volume – Vial 2 | 0.3 mL | 0.65 mL | 1 mL
Folic acid | 42 mcg | 91 mcg | 140 mcg
Biotin | 6 mcg | 13 mcg | 20 mcg
Vitamin B12 (cyanocobalamin) | 0.3 mcg | 0.7 mcg | 1 mcg

INFUVITE PEDIATRIC Pharmacy Bulk Package (see Table 2):

The recommended daily dosage volume of combined content of vials 1 and 2 (1.5 mL, 3.25 mL or 5 mL) is based on the patient’s weight and then added directly to the specific volume of an intravenous fluid [see Dosage and Administration (2.3)].

Table 2: Recommended Weight-Based Dosage of INFUVITE PEDIATRIC Pharmacy Bulk Package
 | Less than 1 kg | 1 kg to less than 3 kg | 3 kg or greater
Daily Dosage Volume(combined contents of Vial 1 and Vial 2) | 1.5 mL | 3.25 mL | 5 mL
Ascorbic acid (Vitamin C) | 24 mg | 52 mg | 80 mg
Vitamin A (as palmitate) | 690 IU (equals 0.2 mg) | 1495 IU (equals 0.5 mg) | 2,300 IU (equals 0.7 mg)
Vitamin D3 (cholecalciferol) | 120 IU (equals 3 mcg) | 260 IU (equals 7 mcg) | 400 IU (equals 10 mcg)
Thiamine (Vitamin B1) (as the hydrochloride) | 0.4 mg | 0.8 mg | 1.2 mg
Riboflavin (Vitamin B2) (as riboflavin 5-phosphate sodium) | 0.4 mg | 0.9 mg | 1.4 mg
Pyridoxine HCl (Vitamin B6) | 0.3 mg | 0.7 mg | 1 mg
Niacinamide | 5.1 mg | 11.1 mg | 17 mg
Dexpanthenol (as d-pantothenyl alcohol) | 1.5 mg | 3.3 mg | 5 mg
Vitamin E (dl-α-tocopheryl acetate) | 2.1 IU (equals 2 mg) | 4.6 IU (equals 5 mg) | 7 IU (equals 7 mg)
Vitamin K1 | 0.1 mg | 0.1 mg | 0.2 mg
Folic acid | 42 mcg | 91 mcg | 140 mcg
Biotin | 6 mcg | 13 mcg | 20 mcg
Vitamin B12 (cyanocobalamin) | 0.3 mcg | 0.7 mcg | 1 mcg

2.3 Preparation and Administration Instructions

Do not administer INFUVITE PEDIATRIC as a direct, undiluted intravenous injection as it may cause dizziness, faintness, and possible tissue irritation.

INFUVITE PEDIATRIC Single Dose:
2. Use only in a suitable work area such as a laminar flow hood (or an equivalent clean air compounding area).
Add one weight-based dose of Vial 1 (1.2 mL, 2.6 mL or 4 mL) and one weight-based dose of Vial 2 (0.3 mL, 0.65 mL or 1 mL) directly to at least 100 mL of intravenous dextrose or saline solution.
4. Discard unused portion.
5. Visually inspect for particulate matter and discoloration prior to administration.
6. After INFUVITE PEDIATRIC is diluted in an intravenous infusion, refrigerate the resulting solution unless it is to be used immediately, and use the solution within 24 hours after dilution.
7. Minimize exposure to light because some of the vitamins in INFUVITE PEDIATRIC, particularly A, D and riboflavin, are light sensitive.
INFUVITE PEDIATRIC Pharmacy Bulk Package:
9. Use only in a suitable work area such as a laminar flow hood (or an equivalent clean air compounding area).
10. Transfer the contents of Vial 2 (10 mL of solution) into the contents of Vial 1 (40 mL of solution). The mixed solution (50 mL) will provide thirty-three 1.5 mL single doses, fifteen 3.25 mL single doses or ten 5 mL single doses.
11. Each bulk vial closure shall be penetrated only one time with a suitable sterile transfer device or dispensing set that allows measured dispensing of the contents.
12. Once the closure system has been penetrated, complete dispensing from the pharmacy bulk vial should be completed within 4 hours. The mixed solution may be refrigerated and stored for up to 4 hours.
13. Discard unused portion.
14. Visually inspect for particulate matter and discoloration prior to administration.
15. Add one dose directly to at least 100 mL of intravenous dextrose or saline solution for each patient.
16. After INFUVITE PEDIATRIC is diluted in an intravenous infusion, refrigerate the resulting solution unless it is to be used immediately, and use the solution within 24 hours after dilution.
17. Minimize exposure to light because some of the vitamins in INFUVITE PEDIATRIC, particularly A, D and riboflavin, are light sensitive.

2.4 Monitoring Vitamin Blood Levels

Blood vitamin concentrations should be monitored to ensure maintenance of adequate levels, particularly in patients receiving parenteral multivitamins as the only source of vitamins for long periods of time.

2.5 Drug Incompatibilities

- INFUVITE PEDIATRIC is not physically compatible with moderately alkaline solutions such as a sodium bicarbonate solution and other alkaline drugs such as acetazolamide sodium, aminophylline, ampicillin sodium, tetracycline HCl and chlorothiazide sodium.
- Folic acid is unstable in the presence of calcium salts such as calcium gluconate.
- Vitamin A and thiamine in INFUVITE PEDIATRIC may react with bisulfite solutions such as sodium bisulfite or vitamin K bisulfite.
- Do not add INFUVITE PEDIATRIC directly to intravenous fat emulsions.
- Consult appropriate references for additional listings of physical and chemical compatibility of solutions and drugs with the vitamin infusion when needed. If incompatibilities are identified, avoid admixture or Y-site administration with vitamin solutions.

3 DOSAGE FORMS AND STRENGTHS

INFUVITE PEDIATRIC Single Dose is an injection consisting of two single-dose vials labeled Vial 1 (4 mL) and Vial 2 (1 mL). For the vitamin strengths [see Dosage and Administration (2.2) and Description (11)].

INFUVITE PEDIATRIC Pharmacy Bulk Package is an injection consisting of two vials labeled Vial 1 (40 mL Fill in 50 mL Vial) and Vial 2 (10 mL). The mixed solution (50 mL) will provide thirty-three 1.5 mL single doses, fifteen 3.25 mL single doses or ten 5 mL single doses. For the vitamin strengths [see Dosage and Administration (2.2) and Description (11)].

4 CONTRAINDICATIONS

INFUVITE PEDIATRIC is contraindicated in patients who have:

- An existing hypervitaminosis, or
- A history of hypersensitivity to any vitamins or excipients contained in this formulation.

5 WARNINGS AND PRECAUTIONS

5.1 Aluminum Toxicity

INFUVITE PEDIATRIC contains aluminum that may be toxic. Aluminum may reach toxic levels with prolonged parenteral administration in pediatric patients with renal impairment. Premature neonates are particularly at risk because their kidneys are immature, and they require large amounts of calcium and phosphate solution, which contain aluminum.

Research indicates that patients with impaired kidney function, including premature neonates who receive parenteral levels of aluminum at greater than 4 to 5 mcg/kg/day accumulate aluminum at levels associated with central nervous system and bone toxicity. Tissue loading may occur at even lower rates of administration. To prevent aluminum toxicity periodically monitor aluminum levels with prolonged parenteral administration of INFUVITE PEDIATRIC.

5.2 Allergic Reactions to Thiamine

Allergic reactions such as urticaria, shortness of breath, wheezing and angioedema have been reported following intravenous administration of thiamine, which is found in INFUVITE PEDIATRIC. There have been rare reports of anaphylaxis following intravenous doses of thiamine. No fatal anaphylaxis associated with INFUVITE PEDIATRIC has been reported.

5.3. Hypervitaminosis A

Hypervitaminosis A, manifested by nausea, vomiting, headache, dizziness, blurred vision has been reported in patients with renal failure receiving 1.5 mg/day retinol and in patients with liver disease. Therefore, supplementation of renal failure patients and patients with liver disease with vitamin A, an ingredient found in INFUVITE PEDIATRIC, should be undertaken with caution [see Use in Specific Populations (8.6, 8.7)]. Blood levels of Vitamin A should be monitored periodically.

5.4 Decreased Anticoagulant Effect of Warfarin

INFUVITE PEDIATRIC contains Vitamin K which may decrease the anticoagulant action of warfarin. In patients who are on warfarin anticoagulant therapy receiving INFUVITE PEDIATRIC monitor blood levels of prothrombin/INR to determine if dose of warfarin needs to be adjusted.

5.5 Interference with Diagnosis of Megaloblastic Anemia

INFUVITE PEDIATRIC contains folic acid and cyanocobalamin which can mask serum deficiencies of folic acid and cyanocobalamin in patients with megaloblastic anemia. Avoid the use of INFUVITE PEDIATRICS in patients with suspected or diagnosed megaloblastic anemia prior to blood sampling for the detection of the folic acid and cyanocobalamin deficiencies.

5.6 Potential to Develop Vitamin Deficiencies or Excesses

In patients receiving parenteral multivitamins such as with INFUVITE PEDIATRIC, blood vitamin concentrations should be periodically monitored to determine if vitamin deficiencies or excesses are developing. INFUVITE PEDIATRIC may not correct long-standing specific vitamin deficiencies. The administration of additional doses of specific vitamins may be required [see Dosage and Administration (2.2)].

5.7 Interference with Urine Glucose Testing

INFUVITE PEDIATRIC contains vitamin C which is also known as ascorbic acid. Ascorbic acid in the urine may cause false negative urine glucose results.

5.8 Vitamin E Overdose in Infants Receiving Additional Vitamin E

Additional vitamin E supplementations of patients receiving INFUVITE PEDIATRIC may result in elevated blood concentrations of vitamin E and potential vitamin E toxicity in infants. Avoid additional oral or parental doses of vitamin E in infants. Daily dose of INFUVITE PEDIATRIC contains adequate concentrations of vitamin E required to achieve normal blood levels of vitamin E.

5.9 Risk of Low Vitamin A Levels

Lower vitamin A concentrations may occur after administration of INFUVITE PEDIATRIC due to the adherence of Vitamin A to plastic. Monitor blood vitamin A concentrations periodically. Additional administration of therapeutic doses of vitamin A may be required, especially in low-birth weight infants.

5.10 Risk of E-Ferol Syndrome in Low-Birth Weight Infants

E-Ferol syndrome manifested by thrombocytopenia, renal dysfunction, hepatomegaly, cholestasis, ascites, hypotension and metabolic acidosis has been reported in low-birth weight infants following administration of polysorbates which are found in INFUVITE PEDIATRIC. No E-Ferol syndrome associated with INFUVITE PEDIATRIC has been reported.

6 ADVERSE REACTIONS

The following adverse reactions are discussed in greater detail in other sections of the labeling.

- Allergic reactions to thiamine [see Warnings and Precautions (5.2)].
- Hypervitaminosis A [see Warnings and Precautions (5.3)]

The following adverse reactions have been identified during postapproval use of INFUVITE PEDIATRIC. Because these reactions are reported voluntarily from a population of uncertain size, it is not always possible to reliably estimate their frequency or establish a causal relationship to drug exposure.

Dermatologic: rash, erythema, pruritis
CNS: headache, dizziness, agitation, anxiety
Ophthalmic: diplopia

7 DRUG INTERACTIONS

A number of interactions between vitamins and drugs have been reported. The following are examples of these types of interactions.

7.1 Drug Interactions Affecting Co-administered Drugs

Warfarin: Vitamin K, a component of INFUVITE PEDIATRIC, antagonizes the anticoagulant action of warfarin. In patients who are co-administered warfarin and INFUVITE PEDIATRIC, blood levels of prothrombin/INR should be monitored to determine if dose of warfarin needs to be adjusted [see Warnings and Precautions (5.4)].
Antibiotics: Thiamine, riboflavin, pyridoxine, niacinamide, and ascorbic acid decrease antibiotic activities of erythromycin, kanamycin, streptomycin, doxycycline, and lincomycin.
Bleomycin: Ascorbic acid and riboflavin inactivate bleomycin in vitro, thus the activity of bleomycin may be reduced.
Levodopa: Pyridoxine may increase the metabolism of levodopa (decrease blood levels of levodopa) and decrease its efficacy.
Phenytoin: Folic acid may increase phenytoin metabolism and lower the serum concentration of phenytoin resulting in increased seizure activity.
Methotrexate: Folic acid may decrease a patient’s response to methotrexate therapy.

7.2 Drug Interactions Affecting Vitamin Levels

Hydralazine, Isoniazid: Concomitant administration of hydralazine or isoniazid may increase pyridoxine requirements.
Phenytoin: Phenytoin may decrease serum folic acid concentrations.

8 USE IN SPECIFIC POPULATIONS

8.1 Pregnancy

Pregnancy Category C.

INFUVITE PEDIATRIC has not been studied in pregnant women. Pregnant women should follow the U.S. recommended daily allowances for pregnancy because their vitamin requirements may exceed those of non-pregnant women. Animal reproduction studies have not been conducted with INFUVITE PEDIATRIC (multiple vitamins injection).

8.3 Nursing Mothers

INFUVITE PEDIATRIC has not been studied in nursing mothers. Lactating women may have vitamin requirements that exceed those of non-lactating women. Caution should be exercised when INFUVITE PEDIATRIC is administered to nursing mothers.

8.4 Pediatric Use

INFUVITE PEDIATRIC is approved for the prevention of vitamin deficiency in pediatric patients up to 11 years old receiving parenteral nutrition. INFUVITE PEDIATRIC has not been studied in pediatric patients older than 11 years.

INFUVITE PEDIATRIC contains aluminum that may be toxic for premature neonates. Aluminum levels should be monitored periodically during administration of INFUVITE PEDIATRIC to premature neonates [see Warnings and Precautions (5.1)].

Additional vitamin E supplementations of infants receiving INFUVITE PEDIATRIC may result in elevated blood concentrations of vitamin E and potential vitamin E toxicity [see Warnings and Precautions (5.8)].

E-Ferol syndrome has been reported in low-birth weight infants following administration of polysorbates which are found in INFUVITE PEDIATRIC. No E-Ferol syndrome associated with INFUVITE PEDIATRIC has been reported [see Warnings and Precautions (5.10)].

8.6 Renal Impairment

INFUVITE PEDIATRIC has not been studied in patients with renal impairment. Monitor renal function, calcium, phosphorus and vitamin A levels in patients with renal impairment [see Warnings and Precautions (5.1, 5.3)].

8.7 Hepatic Impairment

INFUVITE PEDIATRIC has not been studied in patients with liver impairment. Monitor vitamin A levels in patients with liver disease [see Warnings and Precautions (5.3)].

10 OVERDOSAGE

Signs and symptoms of acute or chronic overdosage may be those of individual INFUVITE PEDIATRIC component toxicity. There is no clinical experience with INFUVITE PEDIATRIC overdosage.

11 DESCRIPTION

INFUVITE PEDIATRIC (multiple vitamins injection) is a sterile product consisting of two vials provided as a single dose or as a pharmacy bulk package for intravenous use intended for administration by intravenous infusion after dilution:

INFUVITE PEDIATRIC (multiple vitamins injection) supplied as single dose consists of:

(a) Vial 1 (4 mL); and
(b) Vial 2 (1 mL).

Vial 1 will provide one daily dose of 1.2 mL, 2.6 mL or 4 mL and Vial 2 will provide one daily dose of 0.3 mL, 0.65 mL or 1 mL [see Dosage and Administration (2.2)].

INFUVITE PEDIATRIC (multiple vitamins injection) supplied as pharmacy bulk package consists of:

(a) Vial 1 (40 mL Fill in 50 mL Vial); and
(b) Vial 2 (10 mL).

The mixed solution will provide many single doses [see Dosage and Administration (2.2)].

Each 4 mL of Vial 1 contains 10 vitamins and each 1 mL of Vial 2 contains 3 vitamins (see Table 3).

Table 3: INGREDIENTS IN INFUVITE PEDIATRIC FORMULATION
Vial 1
Active Ingredient | Quantity per 4 mL
Ascorbic acid (Vitamin C) | 80 mg
Vitamin A* (as palmitate) | 2,300 IU (equals 0.7 mg)
Vitamin D3* (cholecalciferol) | 400 IU (equals 10 mcg)
Thiamine (Vitamin B1) (as the hydrochloride) | 1.2 mg
Riboflavin (Vitamin B2) (as riboflavin 5-phosphate sodium) | 1.4 mg
Pyridoxine HCl (Vitamin B6) | 1 mg
Niacinamide | 17 mg
Dexpanthenol (as d-pantothenyl alcohol) | 5 mg
Vitamin E* (dl-α-tocopheryl acetate) | 7 IU (equals 7 mg)
Vitamin K1* | 0.2 mg
*Polysorbate 80 is used to water solubilize the oil-soluble vitamins A, D, E, and K.
Inactive ingredients in 4 mL of Vial 1: 50 mg polysorbate 80, sodium hydroxide and/or hydrochloric acid for pH adjustment, and water for injection.
Vial 2
Active Ingredient | Quantity per 1 mL
Folic acid | 140 mcg
Biotin | 20 mcg
Vitamin B12 (cyanocobalamin) | 1 mcg
Inactive ingredients in 1 mL of Vial 2: 75 mg mannitol, citric acid and/or sodium citrate for pH adjustment and water for injection.

INFUVITE PEDIATRIC (multiple vitamins injection) makes available a combination of oil-soluble and water-soluble vitamins in an aqueous solution, formulated for incorporation into intravenous solutions. The liposoluble vitamins A, D, E, and K have been solubilized in an aqueous medium with polysorbate 80, permitting intravenous administration of these vitamins.

INFUVITE PEDIATRIC contains no more than 30 mcg/L of aluminum (combined Vials 1 and 2).

13 NONCLINICAL TOXICOLOGY

13.1 Carcinogenesis, Mutagenesis, Impairment of Fertility

Carcinogenicity, mutagenicity, and fertility studies have not been performed with INFUVITE PEDIATRIC.

16 HOW SUPPLIED/STORAGE AND HANDLING

How Supplied:

INFUVITE PEDIATRIC (multiple vitamins injection) is supplied as follows:

INFUVITE PEDIATRIC (multiple vitamins injection) Single Dose:

- NDC 54643-9023-1 - Boxes containing ten single dose vials – five each of Vial 1 (4 mL) and five each of Vial 2 (1 mL), one Vial 1 plus one Vial 2 to be used for a single dose [see Dosage and Administration (2.2, 2.3)].

INFUVITE PEDIATRIC (multiple vitamins injection) Pharmacy Bulk Package:

- NDC 54643-9031-0 - Boxes containing two vials – Vial 1 (40 mL Fill in 50 mL Vial) and Vial 2 (10 mL). Mixed contents of Vial 2 with Vial 1 provide thirty-three 1.5 mL single doses, fifteen 3.25 mL single doses or 10 single 5 mL doses [see Dosage and Administration (2.2, 2.3)].

Storage and Handling:

Minimize exposure of INFUVITE PEDIATRIC to light because vitamins A, D and riboflavin are light sensitive.

Store under refrigeration 2° to 8°C (36° to 46°F).

17 PATIENT COUNSELING INFORMATION

Instruct caregiver(s) and patients (if age appropriate):

- To watch for signs of allergic reactions such as urticaria, shortness of breath, wheezing and angioedema since hypersensitivity reactions may occur to any of the vitamins or excipients contained in INFUVITE PEDIATRIC.
- To watch for and immediately report nausea, vomiting, headache, dizziness, blurred vision, especially if patients have renal impairment, as these may be signs of hypervitaminosis A.
- To report other adverse reactions that patients may experience such as rash, erythema, pruritus, headache, dizziness, agitation, anxiety, and diplopia.
- Patients on warfarin anticoagulant therapy will be monitored periodically with blood prothrombin/ INR levels to determine if the dose of warfarin needs to be adjusted.
- About the significance of periodic monitoring of blood vitamin concentrations to determine if vitamin deficiencies or excesses are developing and the need to monitor renal function, calcium, phosphorus, aluminum and vitamin A levels in patients with renal impairment.
- That INFUVITE PEDIATRIC should be avoided in patients with suspected or diagnosed megaloblastic anemia prior to blood sampling for the detection of the folic acid and cyanocobalamin deficiencies.
- That vitamin C (ascorbic acid) contained in INFUVITE PEDIATRIC may cause false negative urine glucose results.

Manufactured by

Sandoz Canada Inc.

145 Jules-Léger Street

Boucherville, Qc, Canada, J4B 7K8

Distributed by

Baxter Healthcare Corporation for NOVAPLUS®

Clintec Nutrition Division

Deerfield, IL 60015 USA

Printed in Canada

NOVAPLUS is a registered trademark of Vizient, Inc.

® INFUVITE is a registered trademark of Sandoz Canada Inc.

46194735

10-2016

Vials Carton

NDC 54643-9023-1 2A9008NP

INFUVITE® PEDiatric

Multiple Vitamins Injection

Rx only

For intravenous infusion after dilution only.

STERILE

Contains 5 each of Vial 1 (4 mL) and Vial 2 (1 mL).

One vial of each to be used for a single dose.

Vial 1

(4 mL)

Vial 2

(1 mL)

Store under refrigeration 2° to 8° C (36° to 46° F).

NOVAPLUS®

Pharmacy Bulk Package Carton

NDC 54643-9031-0 2A9061NP

INFUVITE® PEDiatric

PHARMACY BULK PACKAGE

Multiple Vitamins Injection

Rx only

STERILE

PHARMACY BULK PACKAGE

NOT FOR DIRECT INFUSION

Vial 1

(40 mL fill in 50 mL)

Vial 2

(10 mL)

Both vials combined produce

10 single doses.

For intravenous infusion after dilution only.

Store under refrigeration 2° to 8° C (36° to 46° F).

NOVAPLUS®